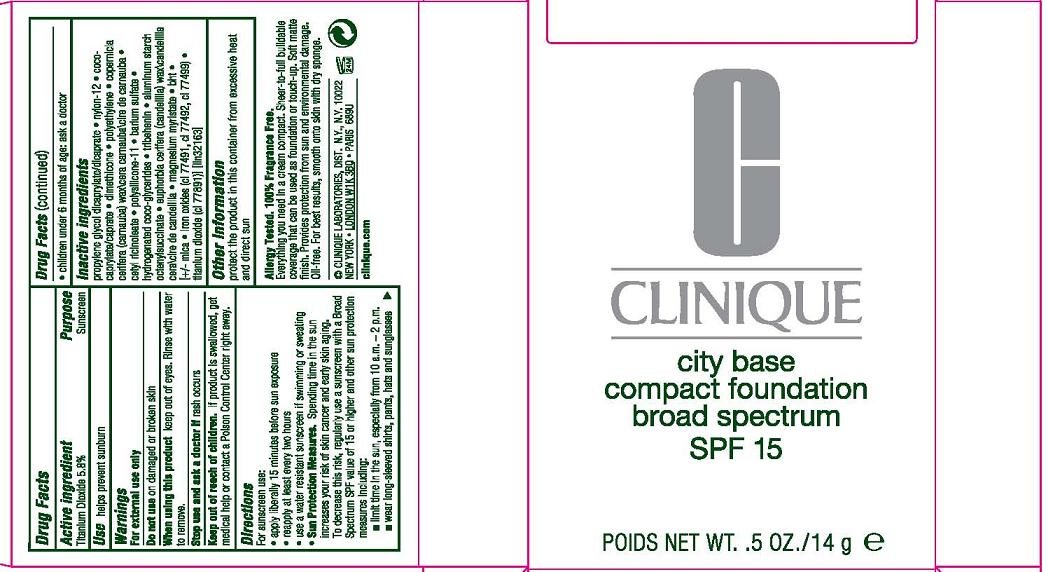 DRUG LABEL: CITY BASE COMPACT FOUNDATION
NDC: 49527-015 | Form: PASTE
Manufacturer: CLINIQUE LABORATORIES INC.
Category: otc | Type: HUMAN OTC DRUG LABEL
Date: 20120619

ACTIVE INGREDIENTS: TITANIUM DIOXIDE 5.8 g/100 g
INACTIVE INGREDIENTS: PROPYLENE GLYCOL DICAPRYLATE/DICAPRATE; COCO-CAPRYLATE/CAPRATE; DIMETHICONE; HIGH DENSITY POLYETHYLENE; CARNAUBA WAX; CETYL RICINOLEATE; BARIUM SULFATE; HYDROGENATED COCO-GLYCERIDES; TRIBEHENIN; ALUMINUM STARCH OCTENYLSUCCINATE; CANDELILLA WAX; MAGNESIUM MYRISTATE; BUTYLATED HYDROXYTOLUENE; MICA; FERRIC OXIDE RED; FERROSOFERRIC OXIDE; FERRIC OXIDE YELLOW

DRUG FACTS

ACTIVE INGREDIENTS:

TITANIUM DIOXIDE 5.8%

PURPOSE

SUNSCREEN

USE

HELPS PREVENT SUNBURN

WARNINGS

FOR EXTERNAL USE ONLY

Do not use on damaged or broken skin

When using this product keep out of eyes. Rinse with water to remove.

Stop use and ask a doctor if rash occurs

Keep out of reach of children.

If product is swallowed, get medical help or contact a Poison Control Center right away.

DIRECTIONS

For sunscreen use:
* apply liberally 15 minutes before sun exposure
* reapply at least every two hours
* use a water resistant sunscreen if swimming or sweating
* Sun Protection Measures.
Spending time in the sun increases your risk of skin cancer and early skin aging. To decrease this risk, regularly use a sunscreen with a Broad Spectrum SPF value of 15 or higher and other sun protection measures including:
o limit time in the sun, especially from 10 a.m.–2 p.m.
o wear long-sleeved shirts, pants, hats and sunglasses
* children under 6 months of age: ask a doctor

INACTIVE INGREDIENTS

ingredients: propylene glycol dicaprylate/dicaprate [] nylon-12 [] coco-caprylate/caprate [] dimethicone [] polyethylene [] copernicia cerifera (carnauba) wax\cera carnauba\cire de carnauba [] cetyl ricinoleate [] polysilicone-11 [] barium sulfate [] hydrogenated coco-glycerides [] tribehenin [] aluminum starch octenylsuccinate [] euphorbia cerifera (candelilla) wax\candelilla cera\cire de candelilla [] magnesium myristate [] bht [] [+/- mica [] iron oxides (ci 77491, ci 77492, ci 77499) [] titanium dioxide (ci 77891)]

OTHER INFORMATION

protect the product in this container from excessive heat and direct sun

PACKAGE LABEL

PRINCIPAL DISPLAY PANEL:

CLINIQUE

CITY BASE

COMPACT FOUNDATION

BROAD SPECTRUM

SPF 15

POIDS NT. WT.0.5 OZ/ 14 g
CLINIQUE LABORATORIES INC DIST
NY NY 10022